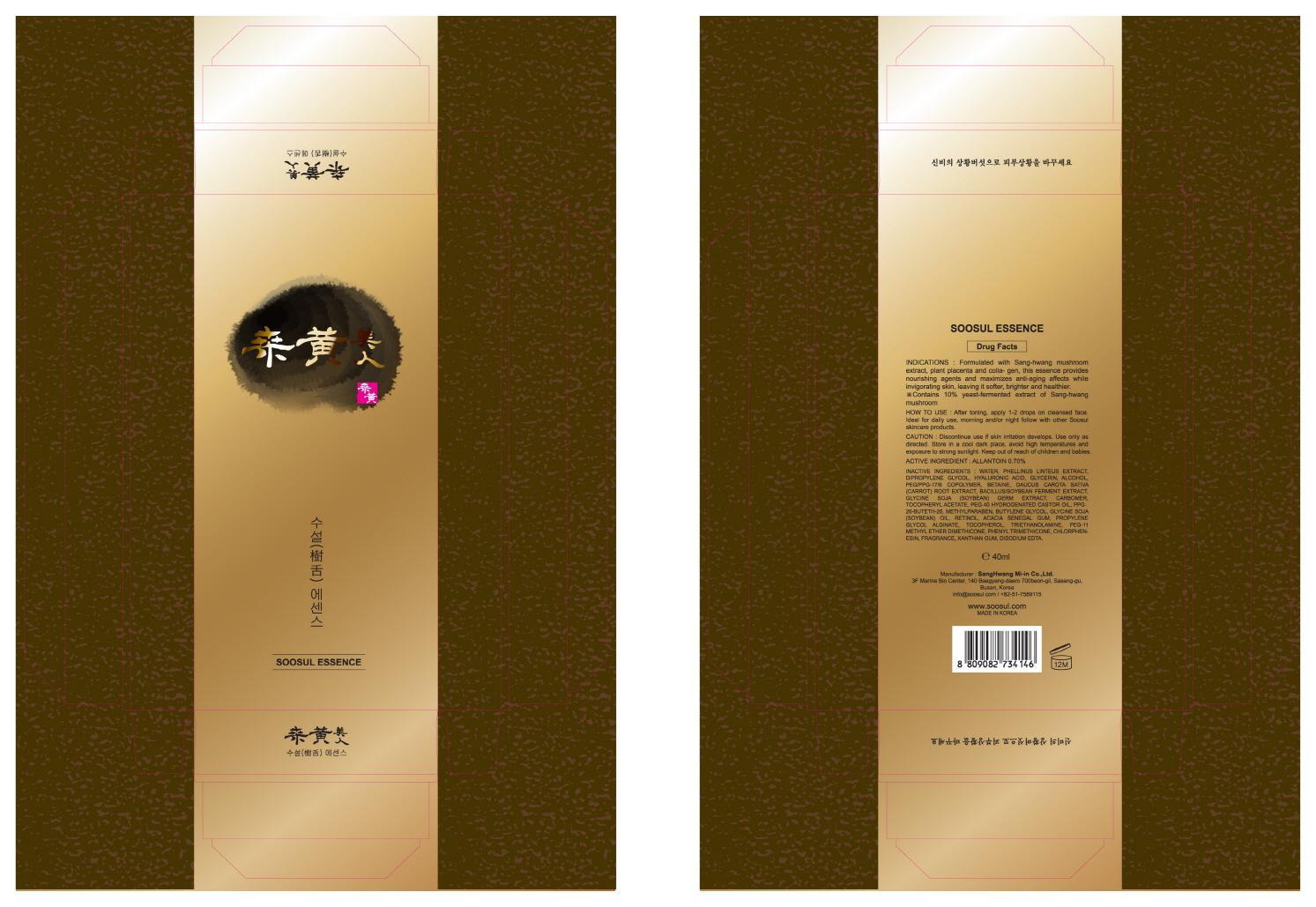 DRUG LABEL: SOOSUL ESSENCE
NDC: 69351-010 | Form: CREAM
Manufacturer: Sang Hwang Mi-in Co., Ltd.
Category: otc | Type: HUMAN OTC DRUG LABEL
Date: 20141127

ACTIVE INGREDIENTS: ALLANTOIN 0.28 mg/40 mL
INACTIVE INGREDIENTS: WATER; DIPROPYLENE GLYCOL

ACTIVE INGREDIENT

Active Ingredient: ALLANTOIN 0.70%

INACTIVE INGREDIENT

Inactive Ingredients:
WATER, PHELLINUS LINTEUS EXTRACT, DIPROPYLENE GLYCOL, HYALURONIC ACID, GLYCERIN, ALCOHOL, PEG/PPG-17/6 COPOLYMER, BETAINE, DAUCUS CAROTA SATIVA (CARROT) ROOT EXTRACT, BACILLUS/SOYBEAN FERMENT EXTRACT, GLYCINE SOJA (SOYBEAN) GERM EXTRACT, CARBOMER, TOCOPHERYL ACETATE, PEG-40 HYDROGENATED CASTOR OIL, PPG-26-BUTETH-26, METHYLPARABEN, BUTYLENE GLYCOL, GLYCINE SOJA (SOYBEAN) OIL, RETINOL, ACACIA SENEGAL GUM, PROPYLENE GLYCOL ALGINATE, TOCOPHEROL, TRIETHANOLAMINE, PEG-11 METHYL ETHER DIMETHICONE, PHENYL TRIMETHICONE, CHLORPHENESIN, FRAGRANCE, XANTHAN GUM, DISODIUM EDTA.

PURPOSE

PURPOSE: SKIN PROTECTANT

Caution

Caution: Discontinue use if skin irritation develops. Use only as directed. Store in a cool dark place, avoid high temperatures and exposure to strong sunlight. Keep out of reach of children and babies.

Keep out of reach of children and babies.

Indications

Formulated with Sang-hwang mushroom extract, plant placenta and collagen, this essence provides nourishing agents and maximizes anti-aging affects while invigorating skin, leaving it softer, brighter and healthier.
- Contains 10% yeast-fermented extract of Sang-hwang mushroom

How to use: After toning, apply 1-2 drops on cleansed face. Ideal for daily use, morning and/or night follow with other Soosul skincare products.